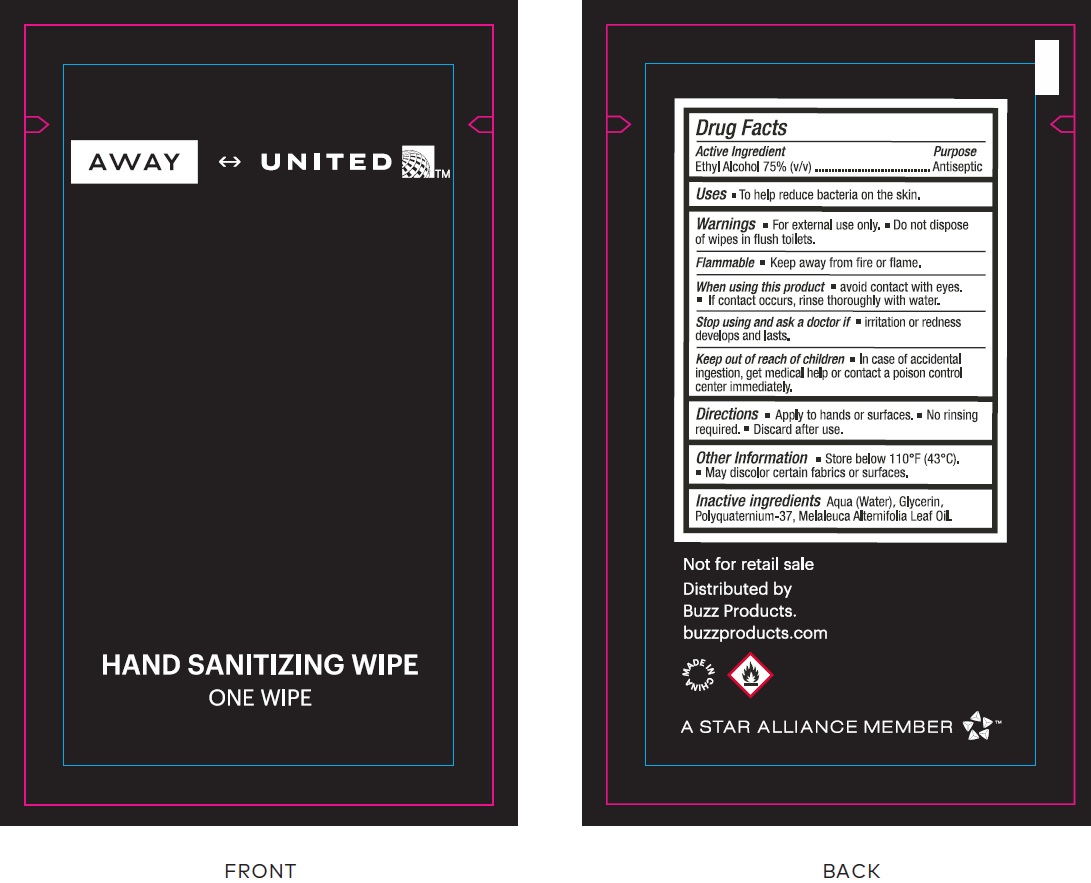 DRUG LABEL: Sanitizer Wipe in Sachet
NDC: 69491-035 | Form: CLOTH
Manufacturer: Buzz Export Services Pty Ltd (Buzz Products)
Category: otc | Type: HUMAN OTC DRUG LABEL
Date: 20231220

ACTIVE INGREDIENTS: ALCOHOL 75 mL/100 mL
INACTIVE INGREDIENTS: WATER; GLYCERIN; TEA TREE OIL

Sanitizer Wipe in Sachet

Active Ingredient

Ethyl Alcohol 75% (v/v)

Purpose

Antiseptic

Uses

- To help reduce bacteria on the skin.

Warnings

- For external use only.
- Do not dispose of wipes in flush toilets.

- Keep away from fire or flame.

Flammable

When using this product

- avoid contact with eyes.
- If contact occurs, rinse thoroughly with water.

Stop using and ask a doctor if

- irritation or redness develops and lasts.

Keep out of reach of children

- In case of accidental ingestion, get medical help or contact a poison control center immediately.

Directions

- Appyl to hands or surface.
- No rinsing required.
- Discard after use.

Other Information

- Store below 110°F (43°C).
- May discolor certain fabrics or surfaces.

Inactive ingredients

Aqua (Water), Glycerin, Polyquaternium-37, Melaleuca Alternifolia Leaf Oil.